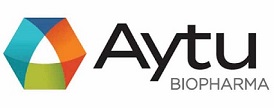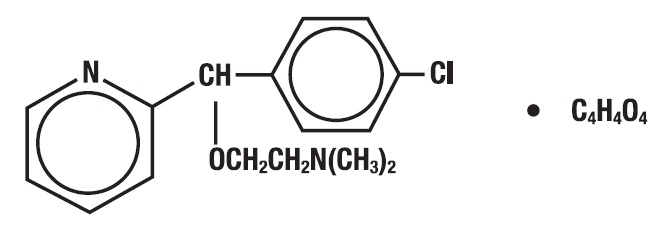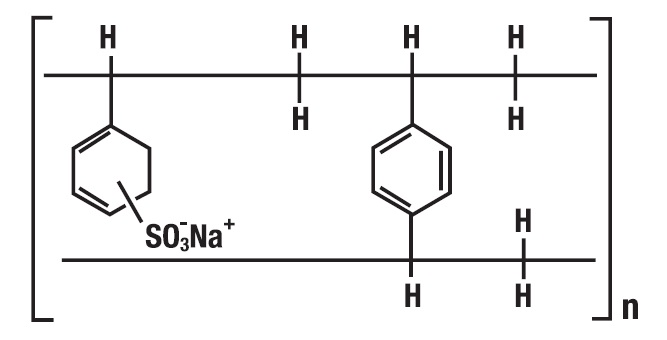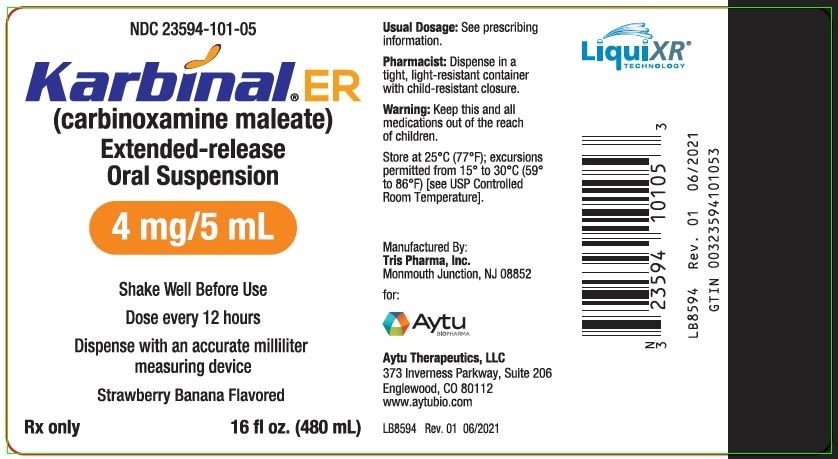 DRUG LABEL: Karbinal
NDC: 23594-101 | Form: SUSPENSION, EXTENDED RELEASE
Manufacturer: Aytu Therapeutics, LLC
Category: prescription | Type: HUMAN PRESCRIPTION DRUG LABEL
Date: 20250108

ACTIVE INGREDIENTS: CARBINOXAMINE MALEATE 4 mg/5 mL
INACTIVE INGREDIENTS: WATER; POLYSORBATE 80; SODIUM METABISULFITE; GLYCERIN; METHYLPARABEN; PROPYLPARABEN; XANTHAN GUM; ANHYDROUS CITRIC ACID; HIGH FRUCTOSE CORN SYRUP; SUCROSE; POVIDONE; SODIUM POLYSTYRENE SULFONATE; TRIACETIN

HIGHLIGHTS OF PRESCRIBING INFORMATION

These highlights do not include all the information needed to use KARBINAL® ER safely and effectively. See full prescribing information for KARBINAL® ER.
Karbinal® ER (carbinoxamine maleate) extended-release oral suspension
Initial U.S. Approval: 1953

RECENT MAJOR CHANGES

Contraindications, Nursing Mothers (4) | Removed 3/2021

1 INDICATIONS AND USAGE

Karbinal ER is indicated for adults and pediatric patients 2 years of age and older for the symptomatic treatment of:

- Seasonal and perennial allergic rhinitis (1)
- Vasomotor rhinitis (1)
- Allergic conjunctivitis due to inhalant allergens and foods (1)
- Mild, uncomplicated allergic skin manifestations of urticaria and angioedema (1)
- Dermatographism (1)
- As therapy for anaphylactic reactions adjunctive to epinephrine and other standard measures after the acute manifestations have been controlled (1)
- Amelioration of the severity of allergic reactions to blood or plasma (1)

2 DOSAGE AND ADMINISTRATION

Adults and Adolescents 12 years of age and older (2.3):

7.5 mL to 20 mL (6 to 16 mg) every 12 hours

Pediatric patients 2-11 years of age (approximately 0.2 to 0.4 mg/kg/day) (2.4):

2 to 3 years – 3.75 mL to 5 mL (3 to 4 mg) every 12 hours

4 to 5 years – 3.75 mL to 10 mL (3 to 8 mg) every 12 hours

6 to 11 years – 7.5 mL to 15 mL (6 to 12 mg) every 12 hours

3 DOSAGE FORMS AND STRENGTHS

Extended-release oral suspension: 4 mg carbinoxamine maleate per 5 mL (3)

4 CONTRAINDICATIONS

- Children younger than 2 years of age (4)
- Patients with known hypersensitivity to the drug or any of the inactive ingredients (4)
- Monoamine oxidase inhibitors (MAOI) (4)

5 WARNINGS AND PRECAUTIONS

- Activities requiring mental alertness: Avoid engaging in hazardous tasks requiring complete mental alertness such as driving or operating machinery. (5.2)
- Anticholinergic actions: Use with caution in patients with increased intraocular pressure, narrow angle glaucoma, hyperthyroidism, cardiovascular disease, hypertension, stenosing peptic ulcer, symptomatic prostatic hypertrophy, bladder neck obstruction, pyloroduodenal obstruction. (5.3)
- Contains sodium metabisulfite, a sulfite that may cause anaphylaxis including life-threatening or less severe asthmatic episodes in susceptible individuals. (5.4)

6 ADVERSE REACTIONS

Most common adverse reactions are: sedation, sleepiness, dizziness, disturbed coordination, epigastric distress, and thickening of bronchial secretions. (6)

To report SUSPECTED ADVERSE REACTIONS, contact Cerecor, Inc., at 1-866-416-9637 or FDA at 1-800-FDA-1088 or www.fda.gov/medwatch.

7 DRUG INTERACTIONS

- Monoamine oxidase inhibitors (MAOIs): Prolong and intensify the anticholinergic (drying) effects. (4 and 7)
- Alcohol and CNS depressants (hypnotics, sedatives, tranquilizers, etc.): Avoid concomitant use due to additive adverse effects. (7)

8 USE IN SPECIFIC POPULATIONS

- Lactation: Advise not to breastfeed. (8.2)
- Contraindicated in children younger than 2 years of age. (4 and 8.4)
- May cause sedation or excitation in young children. (8.4)
- May cause dizziness, sedation, and hypotension in elderly patients. Start elderly patients on lower doses and observe closely for confusion and over-sedation. (8.5)

FULL PRESCRIBING INFORMATION

1 INDICATIONS AND USAGE

Karbinal ER is indicated for adults and pediatric patients 2 years of age and older for the symptomatic treatment of:

- Seasonal and perennial allergic rhinitis
- Vasomotor rhinitis
- Allergic conjunctivitis due to inhalant allergens and foods
- Mild, uncomplicated allergic skin manifestations of urticaria and angioedema
- Dermatographism
- As therapy for anaphylactic reactions adjunctive to epinephrine and other standard measures after the acute manifestations have been controlled
- Amelioration of the severity of allergic reactions to blood or plasma

2 DOSAGE AND ADMINISTRATION

2.1 Overview

The dosage of Karbinal ER should be individualized based on the severity of the condition and the response of the patient. Start with lower doses and increase as needed and tolerated.

2.2 Administration

Administer Karbinal ER by the oral route only. Measure Karbinal ER with an accurate milliliter measuring device. A household teaspoon is not an accurate measuring device and could lead to overdosage. A pharmacist can provide an appropriate measuring device and can provide instructions for measuring correct dose.

2.3 Recommended Dosage for Adults and Adolescents 12 years of age and older:

7.5 mL to 20 mL (6 to 16 mg) every 12 hours administered orally

2.4 Recommended Dosage for Pediatric Patients 2 to 11 years of age (approximately 0.2 to 0.4 mg/kg/day):

2 to 3 years: 3.75 mL to 5 mL (3 to 4 mg) every 12 hours administered orally

4 to 5 years: 3.75 mL to 10 mL (3 to 8 mg) every 12 hours administered orally

6 to 11 years: 7.5 mL to 15 mL (6 to 12 mg) every 12 hours administered orally

3 DOSAGE FORMS AND STRENGTHS

Extended-release oral suspension: 4 mg carbinoxamine maleate per 5 mL

4 CONTRAINDICATIONS

Karbinal ER is contraindicated in:

- children younger than 2 years of age because deaths have been reported in this age group (see Warnings and Precautions (5.1)]
  - patients who are hypersensitive to carbinoxamine maleate or any of the inactive ingredients in Karbinal ER [see Warnings and Precautions (5.1)]
- patients who are taking monoamine oxidase inhibitors (MAOI) [see Drug Interactions(7)].

5 WARNINGS AND PRECAUTIONS

5.1 Pediatric Mortality

Deaths have been reported in children less than 2 years of age who were taking carbinoxamine-containing drug products; therefore, Karbinal ER is contraindicated in children younger than 2 years of age.

5.2 Somnolence and Impaired Mental Alertness

Karbinal ER may produce marked drowsiness and impair the mental or physical abilities required for the performance of potentially hazardous tasks such as driving a car or operating machinery. Advise patients to avoid engaging in hazardous tasks requiring mental alertness and motor coordination after ingestion of Karbinal ER. Avoid concurrent use of Karbinal ER with alcohol or other central nervous system depressants because additional impairment of central nervous system performance may occur.

5.3 Concomitant Medical Conditions

Karbinal ER has anticholinergic (atropine-like) properties and, therefore, should be used with caution in patients with: increased intraocular pressure, narrow angle glaucoma, hyperthyroidism, cardiovascular disease, hypertension, stenosing peptic ulcer, symptomatic prostatic hypertrophy, bladder neck obstruction, or pyloroduodenal obstruction.

5.4 Allergic Reactions due to Sulfites, including Anaphylaxis

Karbinal ER contains sodium metabisulfite, a sulfite that may cause allergic-type reactions, including anaphylaxis and life-threatening or less severe asthmatic episodes, in susceptible individuals. The overall prevalence of sulfite sensitivity in the general population is unknown and probably low. Sulfite sensitivity is seen more frequently in asthmatic than in nonasthmatic individuals.

6 ADVERSE REACTIONS

The following clinically significant adverse reactions are descrived elsewhere in the labeling:

- Somnolense and Impaired Mental Alertness [see Warnings and Precautions (5.2)].
- Allergic Reactions due to Sulfites, including Anaphylaxis [see Warnings and Precautions (5.2)].

The most frequent adverse reactions include: sedation, sleepiness, dizziness, disturbed coordination, epigastric distress, and thickening of bronchial secretions. In clinical use, younger children and older adults may be particularly sensitive to adverse reactions [see Pediatric Use (8.4) and Geriatric Use (8.5)].

The following adverse reactions, listed by body system, have been identified in case reports and during the use of carbinoxamine in observational studies. Because these reactions are reported voluntarily from a population of uncertain size, it is not always possible to reliably estimate their frequency or establish a causal relationship to drug exposure.

Body as a Whole: Urticaria, drug rash, anaphylactic shock, photosensitivity, excessive perspiration, chills, dryness of mouth, nose and throat.

Cardiovascular: Hypotension, headache, palpitations, tachycardia, extrasystoles.

Central Nervous System: Fatigue, confusion, restlessness, excitation, nervousness, tremor, irritability, insomnia, euphoria, paresthesia, blurred vision, diplopia, vertigo, tinnitus, acute labyrinthitis, hysteria, neuritis, convulsions.

Gastrointestinal: Anorexia, nausea, vomiting, diarrhea, constipation.

Hematologic: Hemolytic anemia, thrombocytopenia, agranulocytosis.

Laboratory: Increase in uric acid levels.

Respiratory: Tightness of chest and wheezing, nasal stuffiness.

Urogenital: Urinary frequency, difficult urination, urinary retention, early menses.

7 DRUG INTERACTIONS

- Do not use of Karbinal ER in patients who are taking monoamine oxidase inhibitors (MAOIs), which prolong and intensify the anticholinergic (drying) effects of antihistamines.
- Avoid use of Karbinal ER with alcohol and other CNS depressants (hypnotics, sedatives, tranquilizers, etc.) due to additive effects.

8 USE IN SPECIFIC POPULATIONS

8.1 Pregnancy

Risk Summary

Published data over decades of use of antihistamines, including carbinoxamine, have not identified a drug-associated risk of major birth defects, miscarriage or adverse maternal or fetal out comes. However, published dat a specifically evaluating the risk of carbinoxamine were not found. Animal reproductive studies have not been conducted with carbinoxamine maleate.

The estimated background risk of major birth defects and miscarriage for the indicated population is unknown. All pregnancies have a background risk of birth defect, loss, or other adverse outcomes. In the U.S. general population, the estimated background risks of major birth defects and miscarriage in clinically recognized pregnancies is 2% to 4% and 15% to 20%, respectively.

8.2 Lactation

Risk Summary

Based on the physical properties of carbinoxamine, it is likely that carbinoxamine is present in breastmilk. There are published reports of drowsiness and irritability in infants exposed to antihistamines via breastmilk. There are post-marketing reports of deaths in children under 2 years of age exposed to carbinoxamine by oral administration. There are no available data on the effects on milk production. It is not recommended to breastfeed during treatment wit h Karbinal ER [see Warnings and Precautions (5.1)] and use in Specific Populations (8.4)].

8.4 Pediatric Use

Karbinal ER is contraindicated in pediatric patients younger than 2 years of age becuase deaths have been reported in this patient population who were taking carbinoxamine-containing drug products.

The safety and effectiveness of Karbinal ER in pediatric patients aged 2 years and older hve been established and I based on demonstration of bioequivalence to the immediate-release reference product [see Clinical Phamacology (12.3)]. Carbinoxamine may diminish mental alertness or produce sedation in children. Paradoxical reactions with excitation are more likely in younger children.

8.5 Geriatric Use

Karbinal ER may cause dizziness, hypotension, confusion, or over-sedation in the elderly. Start elderly patients on lower doses and observe closely.

10. OVERDOSAGE

Overdosage with carbinoxamine may cause central nervous system depression or stimulation, hallucinations, convulsions, and death. Atropine-like signs and symptoms – dry mouth; fixed, dilated pupils; flushing; and gastrointestinal symptoms may also occur.

The treatment of overdosage consists of discontinuation of Karbinal ER and institution of symptomatic and supportive therapy. Vital signs (including respiration, pulse, blood pressure, and temperature) and EKG should be monitored. Induction of vomiting is not recommended. Activated charcoal should be given and gastric lavage should be considered after ingestion of a potentially life-threatening amount of drug. In the presence of severe anticholinergic effects, physostigmine may be useful. Vasopressors may be used to treat hypotension.

11. DESCRIPTION

Each 5 mL of Karbinal ER Extended-release Oral Suspension contains carbinoxamine complexed with polistirex equivalent to 4 mg carbinoxamine maleate and the following inactive ingredients: citric acid anhydrous, strawberry-banana flavor, glycerin, high fructose corn syrup, methylparaben, modified food starch, polysorbate 80, polyvinyl acetate, povidone, propylparaben, purified water, sodium metabisulfite, sodium polystyrene sulfonate, sucrose, triacetin, and xanthan gum.

Carbinoxamine maleate is freely soluble in water. The chemical name is 2-[(4-chlorophenyl)-2-pyridinylmethoxy]- N, N-dimethylethanamine (Z)-2-butenedioate (1:1), which has the following structure:

The drug-polistirex complex is formed with the active ingredient (carbinoxamine maleate, USP) and sodium polystyrene sulfonate, USP, which has the following structure:

12. CLINICAL PHARMACOLOGY

12.1 Mechanism of Action

Carbinoxamine is an H1 receptor antagonist (antihistamine) that exhibits anticholinergic (drying) and sedative properties.

Antihistamines compete with histamine for receptor sites on effector cells.

12.3 Pharmacokinetics

Karbinal ER after single-dose administration of 16 mg was bioequivalent to the reference carbinoxamine immediate-release oral solution after the administration of two doses of 8 mg six hours apart under fasting conditions. The carbinoxamine mean (SD) peak plasma concentration (Cmax) was 28.7 (5.3) ng/mL at 6.7 hours after Karbinal ER administration. The plasma half-life of carbinoxamine was 17.0 hours. There was no effect of food on the pharmacokinetic parameters.

Karbinal ER after multiple-dose administration of 16 mg every 12 hours for 8 days was bioequivalent to the reference carbinoxamine immediate-release oral solution after multiple-dose administration of 8 mg every 6 hours. The mean (SD) steady-state Cmax was 72.9 (24.4) ng/mL at 5.6 hours after Karbinal ER administration. Carbinoxamine mean (SD) minimum plasma concentration at steady-state was 51.8 (20.3) ng/mL.

13. NONCLINICAL TOXICOLOGY

13.1. Carcinogenesis, Mutagenesis, Impairment of Fertility

No long-term studies in animals have been performed to determine the possible effects of carbinoxamine on carcinogenesis, mutagenesis, and fertility.

14. CLINICAL STUDIES

The effectiveness and safety of Karbinal ER is based on demonstration of bioequivalence to the immediate-release reference product [see Pharmacokinetics (12.3)].

16. HOW SUPPLIED/STORAGE AND HANDLING

Karbinal ER Oral Suspension contains 4 mg carbinoxamine maleate per 5 mL. It is a light beige to tan viscous suspension with strawberry-banana flavor and is supplied as follows:

NDC 23594-101-05 Bottles of 16 fl oz (480 mL)
NDC 23594-101-01 Bottles of 1 fl oz (30 mL) Physician Samples

STORAGE AND HANDLING

Store at 25°C (77°F); excursions permitted from 15° to 30°C (59° to 86°F). [See USP Controlled Room Temperature.]

Dispense in tight, light-resistant container with child-resistant closure.

17. Patient Counseling Information

Administration

Advise patients to measure Karbinal ER with an accurate milliliter measuring device. A household teaspoon is not an accurate measuring device and could lead to overdosage. [see Dosage and Administration (2.2)].

Activities Requiring Mental Alertness

Advise patients to use caution when driving a motor vehicle or operating machinery. Karbinal ER may produce marked drowsiness and impair the mental or physical abilities required for the performance of potentially hazardous tasks such as driving a car or operating machinery [see Warnings and Precautions (5.2)].

MAOIs

Advise patients to not use MAOIs while taking Karbinal ER. MAOIs may prolong and intensify the anticholinergic (drying) effects [see Contraindications (4.4) and Drug Interactions (7)].

Lactation

Advise women that breastfeeding is not recommended during treatment with Karbinal ER [see Warnings and Precautions (5.1) and Use in Specific Populations (8.2 and 8.4)].

PRINCIPAL DISPLAY PANEL - 480 mL Bottle Label

NDC 23594-101-05

Karbinal™ ER
(carbinoxamine maleate)
Extended-release
Oral Suspension

4 mg/5 ml

Shake Well Before Use

Dose every 12 hours

Dispense with an accurate
milliliter measuring device

Strawberry Banana Flavored

Rx only 16 fl oz. (480 mL)

Manufactured by:
Tris Pharma, Inc.
Monmouth Junction, NJ 08852

Distributed by:

Aytu Therapeutics
Englewood, CO 80112
www.aytubio.com

LB8594
Rev 01
06/2021